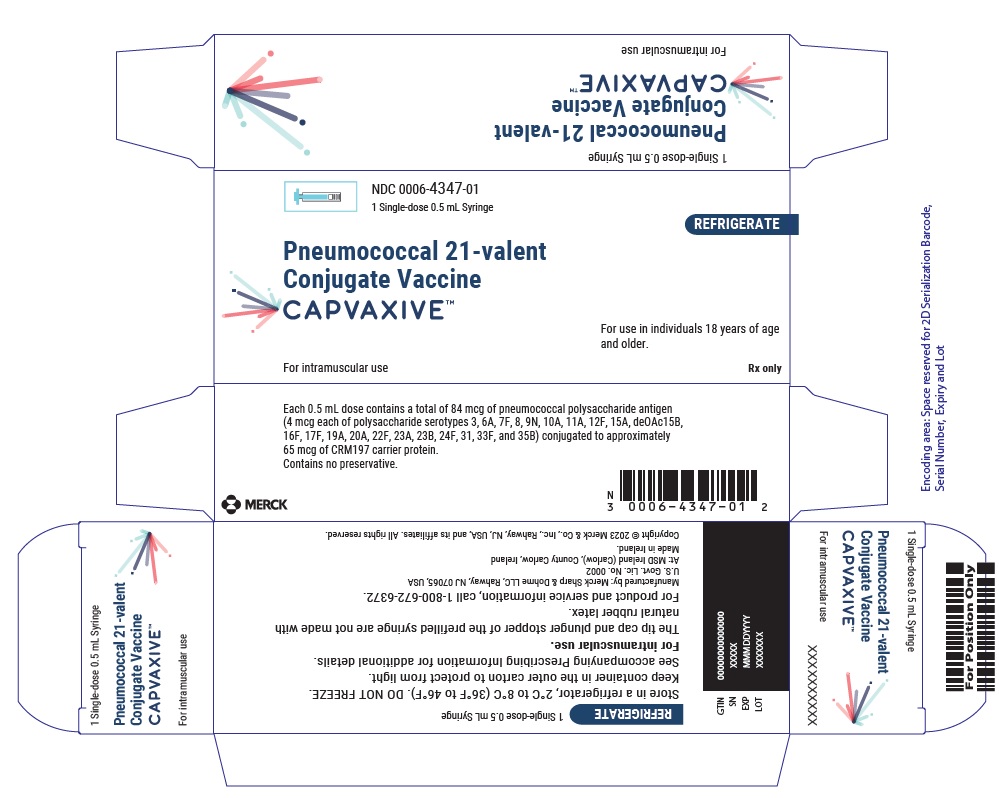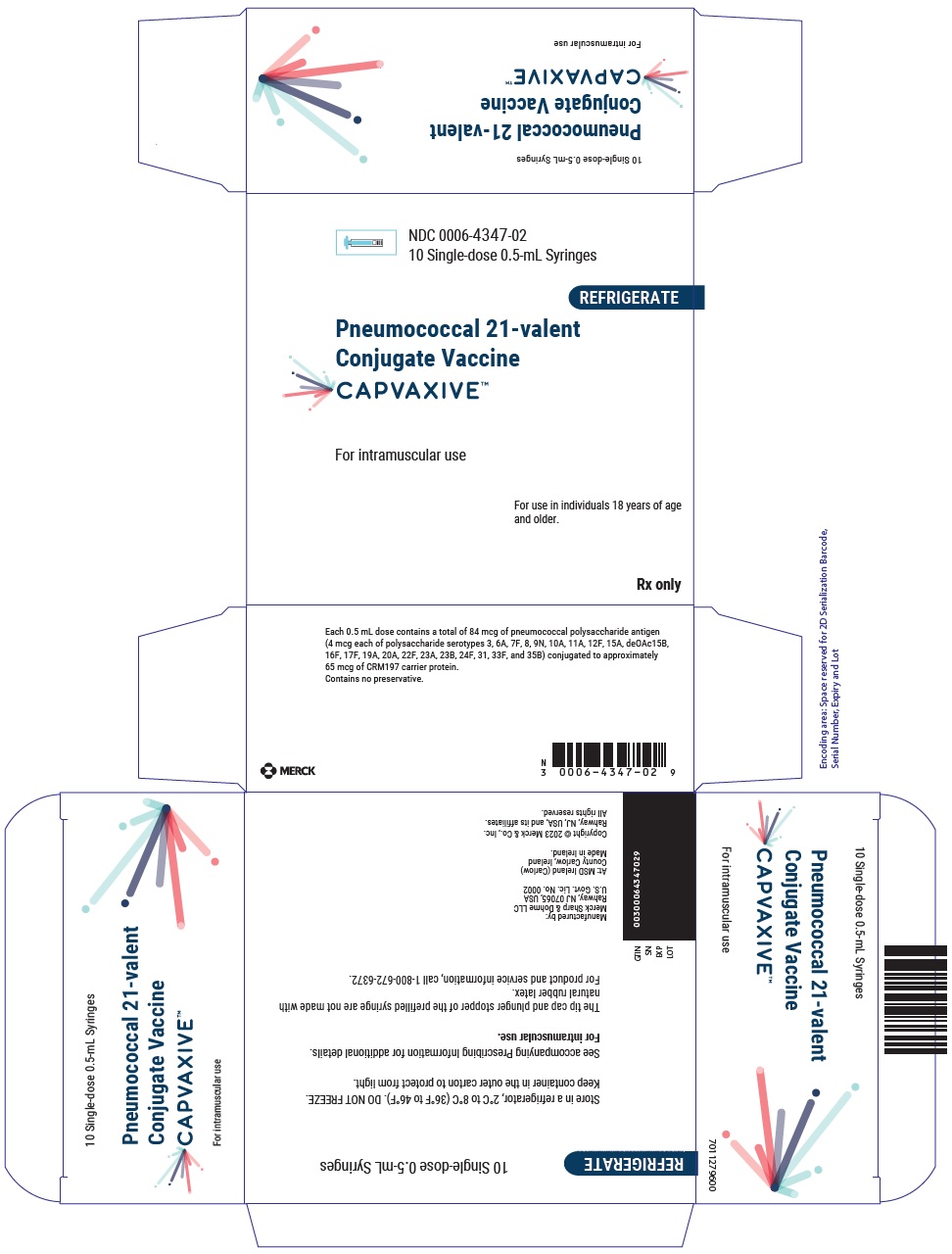 DRUG LABEL: CAPVAXIVE
NDC: 0006-4347 | Form: INJECTION, SOLUTION
Manufacturer: Merck Sharp & Dohme LLC
Category: other | Type: VACCINE LABEL
Date: 20250731

ACTIVE INGREDIENTS: STREPTOCOCCUS PNEUMONIAE TYPE 3 CAPSULAR POLYSACCHARIDE DIPHTHERIA CRM197 PROTEIN CONJUGATE ANTIGEN 4 ug/0.5 mL; STREPTOCOCCUS PNEUMONIAE TYPE 6A CAPSULAR POLYSACCHARIDE DIPHTHERIA CRM197 PROTEIN CONJUGATE ANTIGEN 4 ug/0.5 mL; STREPTOCOCCUS PNEUMONIAE TYPE 7F CAPSULAR POLYSACCHARIDE DIPHTHERIA CRM197 PROTEIN CONJUGATE ANTIGEN 4 ug/0.5 mL; STREPTOCOCCUS PNEUMONIAE TYPE 8 CAPSULAR POLYSACCHARIDE DIPHTHERIA CRM197 PROTEIN CONJUGATE ANTIGEN 4 ug/0.5 mL; STREPTOCOCCUS PNEUMONIAE TYPE 9N CAPSULAR POLYSACCHARIDE DIPHTHERIA CRM197 PROTEIN CONJUGATE ANTIGEN 4 ug/0.5 mL; STREPTOCOCCUS PNEUMONIAE TYPE 10A CAPSULAR POLYSACCHARIDE DIPHTHERIA CRM197 PROTEIN CONJUGATE ANTIGEN 4 ug/0.5 mL; STREPTOCOCCUS PNEUMONIAE TYPE 11A CAPSULAR POLYSACCHARIDE DIPHTHERIA CRM197 PROTEIN CONJUGATE ANTIGEN 4 ug/0.5 mL; STREPTOCOCCUS PNEUMONIAE TYPE 12F CAPSULAR POLYSACCHARIDE DIPHTHERIA CRM197 PROTEIN CONJUGATE ANTIGEN 4 ug/0.5 mL; STREPTOCOCCUS PNEUMONIAE TYPE 15A CAPSULAR POLYSACCHARIDE DIPHTHERIA CRM197 PROTEIN CONJUGATE ANTIGEN 4 ug/0.5 mL; STREPTOCOCCUS PNEUMONIAE TYPE DEOAC15B CAPSULAR POLYSACCHARIDE DIPHTHERIA CRM197 PROTEIN CONJUGATE ANTIGEN 4 ug/0.5 mL; STREPTOCOCCUS PNEUMONIAE TYPE 16F CAPSULAR POLYSACCHARIDE DIPHTHERIA CRM197 PROTEIN CONJUGATE ANTIGEN 4 ug/0.5 mL; STREPTOCOCCUS PNEUMONIAE TYPE 17F CAPSULAR POLYSACCHARIDE DIPHTHERIA CRM197 PROTEIN CONJUGATE ANTIGEN 4 ug/0.5 mL; STREPTOCOCCUS PNEUMONIAE TYPE 19A CAPSULAR POLYSACCHARIDE DIPHTHERIA CRM197 PROTEIN CONJUGATE ANTIGEN 4 ug/0.5 mL; STREPTOCOCCUS PNEUMONIAE TYPE 20A CAPSULAR POLYSACCHARIDE DIPHTHERIA CRM197 PROTEIN CONJUGATE ANTIGEN 4 ug/0.5 mL; STREPTOCOCCUS PNEUMONIAE TYPE 22F CAPSULAR POLYSACCHARIDE DIPHTHERIA CRM197 PROTEIN CONJUGATE ANTIGEN 4 ug/0.5 mL; STREPTOCOCCUS PNEUMONIAE TYPE 23A CAPSULAR POLYSACCHARIDE DIPHTHERIA CRM197 PROTEIN CONJUGATE ANTIGEN 4 ug/0.5 mL; STREPTOCOCCUS PNEUMONIAE TYPE 23B CAPSULAR POLYSACCHARIDE DIPHTHERIA CRM197 PROTEIN CONJUGATE ANTIGEN 4 ug/0.5 mL; STREPTOCOCCUS PNEUMONIAE TYPE 24F CAPSULAR POLYSACCHARIDE DIPHTHERIA CRM197 PROTEIN CONJUGATE ANTIGEN 4 ug/0.5 mL; STREPTOCOCCUS PNEUMONIAE TYPE 31 CAPSULAR POLYSACCHARIDE DIPHTHERIA CRM197 PROTEIN CONJUGATE ANTIGEN 4 ug/0.5 mL; STREPTOCOCCUS PNEUMONIAE TYPE 33F CAPSULAR POLYSACCHARIDE DIPHTHERIA CRM197 PROTEIN CONJUGATE ANTIGEN 4 ug/0.5 mL; STREPTOCOCCUS PNEUMONIAE TYPE 35B CAPSULAR POLYSACCHARIDE DIPHTHERIA CRM197 PROTEIN CONJUGATE ANTIGEN 4 ug/0.5 mL; CORYNEBACTERIUM DIPHTHERIAE CRM197 PROTEIN 65 ug/0.5 mL
INACTIVE INGREDIENTS: HISTIDINE; POLYSORBATE 20; SODIUM CHLORIDE; WATER

HIGHLIGHTS OF PRESCRIBING INFORMATION

These highlights do not include all the information needed to use CAPVAXIVE safely and effectively. See full prescribing information for CAPVAXIVE.
CAPVAXIVE™ (Pneumococcal 21-valent Conjugate Vaccine)
injection, for intramuscular use
Initial U.S. Approval: 2024

1 INDICATIONS AND USAGE

CAPVAXIVE™ is a vaccine indicated for:

- active immunization for the prevention of invasive disease caused by Streptococcus pneumoniae serotypes 3, 6A, 7F, 8, 9N, 10A, 11A, 12F, 15A, 15B, 15C, 16F, 17F, 19A, 20A, 22F, 23A, 23B, 24F, 31, 33F, and 35B in individuals 18 years of age and older. (1)
- active immunization for the prevention of pneumonia caused by S. pneumoniae serotypes 3, 6A, 7F, 8, 9N, 10A, 11A, 12F, 15A, 15C, 16F, 17F, 19A, 20A, 22F, 23A, 23B, 24F, 31, 33F, and 35B in individuals 18 years of age and older. (1)

The indication for the prevention of pneumonia caused by S. pneumoniae serotypes 3, 6A, 7F, 8, 9N, 10A, 11A, 12F, 15A, 15C, 16F, 17F, 19A, 20A, 22F, 23A, 23B, 24F, 31, 33F, and 35B is approved under accelerated approval based on immune responses as measured by opsonophagocytic activity (OPA). Continued approval for this indication may be contingent upon verification and description of clinical benefit in a confirmatory trial. (1)

2 DOSAGE AND ADMINISTRATION

For intramuscular use.

- Administer a single 0.5 mL dose. (2.1)

3 DOSAGE FORMS AND STRENGTHS

CAPVAXIVE is an injection. A single dose is 0.5 mL. (3)

4 CONTRAINDICATIONS

Severe allergic reaction (e.g., anaphylaxis) to any component of CAPVAXIVE or to diphtheria toxoid. (4)

6 ADVERSE REACTIONS

The most commonly reported (>10%) solicited adverse reactions:

- in individuals 18 through 49 years of age were: injection-site pain (73.1%), fatigue (36.0%), headache (27.5%), myalgia (16.4%), injection-site erythema (13.8%), and injection-site swelling (13.3%). (6.1)
- in individuals 50 years of age and older were: injection-site pain (41.2%), fatigue (19.7%), and headache (11.0%). (6.1)

To report SUSPECTED ADVERSE REACTIONS, contact Merck Sharp & Dohme LLC at 1-877-888-4231 or VAERS at 1-800-822-7967 or www.vaers.hhs.gov .

FULL PRESCRIBING INFORMATION

1 INDICATIONS AND USAGE

CAPVAXIVE™ is indicated for:

- active immunization for the prevention of invasive disease caused by Streptococcus pneumoniae serotypes 3, 6A, 7F, 8, 9N, 10A, 11A, 12F, 15A, 15B, 15C, 16F, 17F, 19A, 20A, 22F, 23A, 23B, 24F, 31, 33F, and 35B in individuals 18 years of age and older.
- active immunization for the prevention of pneumonia caused by S. pneumoniae serotypes 3, 6A, 7F, 8, 9N, 10A, 11A, 12F, 15A, 15C, 16F, 17F, 19A, 20A, 22F, 23A, 23B, 24F, 31, 33F, and 35B in individuals 18 years of age and older.

The indication for the prevention of pneumonia caused by S. pneumoniae serotypes 3, 6A, 7F, 8, 9N, 10A, 11A, 12F, 15A, 15C, 16F, 17F, 19A, 20A, 22F, 23A, 23B, 24F, 31, 33F, and 35B is approved under accelerated approval based on immune responses as measured by opsonophagocytic activity (OPA) [See Clinical Studies (14.1)]. Continued approval for this indication may be contingent upon verification and description of clinical benefit in a confirmatory trial.

2 DOSAGE AND ADMINISTRATION

For intramuscular use.

2.1 Dosage

Administer a single 0.5 mL dose.

2.2 Administration

CAPVAXIVE is a colorless, clear to opalescent solution. Parenteral drug products should be inspected visually for particulate matter and discoloration prior to administration, whenever solution and container permit. Do not use if particulate matter or discoloration is observed. Administer intramuscularly.

3 DOSAGE FORMS AND STRENGTHS

CAPVAXIVE is an injection. A single dose is 0.5 mL.

4 CONTRAINDICATIONS

Do not administer CAPVAXIVE to individuals with a history of a severe allergic reaction (e.g., anaphylaxis) to any component of CAPVAXIVE or to diphtheria toxoid. [See Description (11).]

5 WARNINGS AND PRECAUTIONS

5.1 Management of Allergic Reactions

Appropriate medical treatment must be immediately available to manage potential anaphylactic reactions following administration of CAPVAXIVE.

5.2 Altered Immunocompetence

Individuals with altered immunocompetence, including those receiving immunosuppressive therapy, may have a reduced immune response to CAPVAXIVE.

6 ADVERSE REACTIONS

6.1 Clinical Trials Experience

Because clinical trials are conducted under widely varying conditions, adverse reaction rates observed in the clinical trials of a vaccine cannot be directly compared with rates in the clinical trials of another vaccine and may not reflect the rates observed in practice.

The most commonly reported (>10%) solicited adverse reactions in individuals 18 through 49 years of age who received CAPVAXIVE were: injection-site pain (73.1%), fatigue (36.0%), headache (27.5%), myalgia (16.4%), injection-site erythema (13.8%), and injection-site swelling (13.3%).

The most commonly reported (>10%) solicited adverse reactions in individuals 50 years of age and older who received CAPVAXIVE were: injection-site pain (41.2%), fatigue (19.7%), and headache (11.0%).

Safety Assessment in Clinical Studies

The safety of CAPVAXIVE was assessed in four clinical studies (Studies 1-4) conducted across the Americas, Europe, and Asia Pacific, which included individuals ranging in age from 18 through 97 years. Across all 4 studies, 4,556 individuals received CAPVAXIVE and 2,021 individuals received an active comparator vaccine.

The safety of CAPVAXIVE was assessed in individuals 19 through 86 years of age living with HIV who are at increased risk for pneumococcal disease (Study 5). In Study 5, 155 individuals received CAPVAXIVE and 157 individuals received comparator vaccines.

The safety of CAPVAXIVE was assessed in pneumococcal vaccine-naïve individuals 18 through 64 years of age at increased risk for pneumococcal disease due to one or more prespecified medical conditions (diabetes mellitus, chronic heart disease, chronic kidney disease, chronic liver disease, chronic lung disease) (Study 6). In Study 6 386 individuals received CAPVAXIVE and 130 individuals received comparator vaccines.

In all studies, safety was monitored using an electronic Vaccination Report Card for 30 days postvaccination. Injection-site adverse reactions, systemic adverse reactions, and body temperature were solicited Day 1 through Day 5 postvaccination. Unsolicited adverse events were reported Day 1 through Day 30 postvaccination. Serious adverse events (SAEs) were reported through 6 months postvaccination in all studies.

Demographics of Individuals in Clinical Studies

Across Studies 1-4, the mean age of the individuals who were randomized and vaccinated was 53.5 years, and 57.2% were female. The racial distribution was as follows: 76.0% were White, 10.2% were Black or African American, 9.9% were Asian, and 0.5% were American Indian or Alaska Native; 20.6% were of Hispanic or Latino ethnicity. Approximately 34% of vaccinated individuals had one or more prespecified chronic medical conditions known to increase the risk of pneumococcal disease (i.e., diabetes, renal disorders, chronic heart disease, chronic liver disease, chronic lung disease including asthma, smoking, alcoholism).

In Study 6, in individuals with one or more prespecified medical conditions, the mean age of those who were randomized and vaccinated was 52.6 years and 45.2% were female. The racial distribution was as follows: 76.6% were White, 3.5% were Black or African American, 14.3% were Asian, and 0.2% were American Indian or Alaska Native; 26.4% were of Hispanic or Latino ethnicity.

Pneumococcal Vaccine-Naïve Individuals 18 years of Age and Older

In a double-blind study, Study 1 (NCT05425732), individuals 18 years of age and older who had not previously received a pneumococcal vaccine were enrolled and randomized to receive a single dose of CAPVAXIVE or Prevnar 20. The percentage of individuals 18 through 49 years of age and 50 years of age and older who reported solicited adverse reactions that occurred within 5 days postvaccination of CAPVAXIVE or Prevnar 20 is shown in Table 1. Solicited adverse reactions following administration of CAPVAXIVE lasted a median of 2 days with 81.3% of reactions lasting ≤3 days for individuals 18 through 49 years of age and a median of 1 day with 86.5% of reactions lasting ≤3 days for individuals 50 years of age and older.

Table 1: Individuals With Solicited Local and Systemic Adverse Reactions Within 5 Days Postvaccination in Pneumococcal Vaccine-Naïve Individuals 18 through 49 Years of Age and 50 Years of Age and Older – Study 1
 |  | 18 through 49 Years of Age |  | 50 Years of Age and older
 |  | CAPVAXIVE n (%) | Prevnar 20 n (%) | CAPVAXIVE n (%) | Prevnar 20 n (%)
Individuals in population [Every individual is counted a single time for each applicable row and column.] |  | 200 | 100 | 1177 | 1175
Local adverse reactions [Injection-site erythema, injection-site pain, injection-site swelling, fatigue, headache, and myalgia were solicited from Day 1 through Day 5 postvaccination.] | Severity
Pain | Any | 143 (71.5) | 74 (74.0) | 464 (39.4) | 607 (51.7)
Pain | Mild | 95 (47.5) | 49 (49.0) | 361 (30.7) | 504 (42.9)
Pain | Moderate | 46 (23.0) | 25 (25.0) | 102 (8.7) | 102 (8.7)
Pain | Severe | 2 (1.0) | 0 | 1 (0.1) | 1 (0.1)
Erythema | Any | 31 (15.5) | 13 (13.0) | 64 (5.4) [Includes one individual with an event of missing / unknown intensity.] | 74 (6.3)
Erythema | Mild (≤5.0 cm) | 23 (11.5) | 10 (10.0) | 51 (4.3) | 59 (5.0)
Erythema | Moderate (>5.0 to ≤10.0 cm) | 7 (3.5) | 3 (3.0) | 10 (0.8) | 12 (1.0)
Erythema | Severe (>10.0 cm) | 1 (0.5) | 0 | 2 (0.2) | 2 (0.2)
Swelling | Any | 28 (14.0) | 14 (14.0) | 71 (6.0) | 98 (8.3)
Swelling | Mild (≤5.0 cm) | 20 (10.0) | 9 (9.0) | 53 (4.5) | 79 (6.7)
Swelling | Moderate (>5.0 to ≤10.0 cm) | 7 (3.5) | 5 (5.0) | 15 (1.3) | 17 (1.4)
Swelling | Severe (>10.0 cm) | 1 (0.5) | 0 | 3 (0.3) | 2 (0.2)
Systemic adverse reactions | Severity
Fatigue | Any | 81 (40.5) | 34 (34.0) | 237 (20.1) | 230 (19.6)
Fatigue | Mild | 50 (25.0) | 21 (21.0) | 167 (14.2) | 153 (13.0)
Fatigue | Moderate | 29 (14.5) | 11 (11.0) | 70 (5.9) | 72 (6.1)
Fatigue | Severe | 2 (1.0) | 2 (2.0) | 0 | 5 (0.4)
Headache | Any | 59 (29.5) | 24 (24.0) | 135 (11.5) | 152 (12.9)
Headache | Mild | 44 (22.0) | 17 (17.0) | 102 (8.7) | 106 (9.0)
Headache | Moderate | 14 (7.0) | 7 (7.0) | 33 (2.8) | 45 (3.8)
Headache | Severe | 1 (0.5) | 0 | 0 | 1 (0.1)
Myalgia | Any | 33 (16.5) | 14 (14.0) | 70 (5.9) | 79 (6.7)
Myalgia | Mild | 15 (7.5) | 9 (9.0) | 40 (3.4) | 42 (3.6)
Myalgia | Moderate | 15 (7.5) | 4 (4.0) | 30 (2.5) | 36 (3.1)
Myalgia | Severe | 3 (1.5) | 1 (1.0) | 0 | 1 (0.1)
Pyrexia [Pyrexia was defined as temperature ≥38.0°C (100.4°F) solicited from Day 1 through Day 5 postvaccination. Percentages are based on the number of individuals with temperature data: 18 through 49 years of age: CAPVAXIVE, n=199, Prevnar 20, n=100. 50 years of age and older: CAPVAXIVE, n=1169, Prevnar 20, n=1170.] | ≥38.0°C (100.4°F) | 7 (3.5) | 1 (1.0) | 15 (1.3) | 15 (1.3)
Pyrexia [Pyrexia was defined as temperature ≥38.0°C (100.4°F) solicited from Day 1 through Day 5 postvaccination. Percentages are based on the number of individuals with temperature data: 18 through 49 years of age: CAPVAXIVE, n=199, Prevnar 20, n=100. 50 years of age and older: CAPVAXIVE, n=1169, Prevnar 20, n=1170.] | ≥38.0°C (100.4°F) to <38.5°C (101.3°F) | 3 (1.5) | 0 | 7 (0.6) | 7 (0.6)
Pyrexia [Pyrexia was defined as temperature ≥38.0°C (100.4°F) solicited from Day 1 through Day 5 postvaccination. Percentages are based on the number of individuals with temperature data: 18 through 49 years of age: CAPVAXIVE, n=199, Prevnar 20, n=100. 50 years of age and older: CAPVAXIVE, n=1169, Prevnar 20, n=1170.] | ≥38.5°C (101.3°F) to <39.0°C (102.2°F) | 2 (1.0) | 0 | 6 (0.5) | 5 (0.4)
Pyrexia [Pyrexia was defined as temperature ≥38.0°C (100.4°F) solicited from Day 1 through Day 5 postvaccination. Percentages are based on the number of individuals with temperature data: 18 through 49 years of age: CAPVAXIVE, n=199, Prevnar 20, n=100. 50 years of age and older: CAPVAXIVE, n=1169, Prevnar 20, n=1170.] | ≥39.0°C (102.2°F) | 2 (1.0) | 1 (1.0) | 2 (0.2) | 3 (0.3)
Mild: does not interfere with activity; Moderate: interferes with activity; Severe: prevents daily activity.

In Study 2 (NCT05464420), individuals 18 through 49 years of age who had not previously received a pneumococcal vaccine were enrolled and randomized to receive a single dose of CAPVAXIVE or PNEUMOVAX 23. The percentage of individuals 18 through 49 years of age with solicited adverse reactions that occurred within 5 days postvaccination of CAPVAXIVE or PNEUMOVAX 23 is shown in Table 2.

Table 2: Individuals with Solicited Local and Systemic Adverse Reactions Within 5 Days Postvaccination in Pneumococcal Vaccine-Naïve Individuals 18 through 49 Years of Age – Study 2
 |  | CAPVAXIVE n (%) | PNEUMOVAX 23 n (%)
Individuals in population [Every individual is counted a single time for each applicable row and column.] |  | 1,616 | 541
Local adverse reactions [Injection-site erythema, injection-site pain, injection-site swelling, fatigue, headache, and myalgia were solicited from Day 1 through Day 5 postvaccination.] | Severity
Pain | Any | 1,184 (73.3) | 328 (60.6)
Pain | Mild | 759 (47.0) | 234 (43.3)
Pain | Moderate | 395 (24.4) | 86 (15.9)
Pain | Severe | 30 (1.9) | 8 (1.5)
Erythema | Any | 219 (13.6) | 41 (7.6)
Erythema | Mild (≤5.0 cm) | 143 (8.8) | 30 (5.5)
Erythema | Moderate (>5.0 to ≤10.0 cm) | 57 (3.5) | 8 (1.5)
Erythema | Severe (>10.0 cm) | 19 (1.2) | 3 (0.6)
Swelling | Any | 213 (13.2) | 41 (7.6)
Swelling | Mild (≤5.0 cm) | 148 (9.2) | 29 (5.4)
Swelling | Moderate (>5.0 to ≤10.0 cm) | 55 (3.4) | 10 (1.8)
Swelling | Severe (>10.0 cm) | 10 (0.6) | 2 (0.4)
Systemic adverse reactions | Severity
Fatigue | Any | 573 (35.5) | 184 (34.0)
Fatigue | Mild | 338 (20.9) | 119 (22.0)
Fatigue | Moderate | 201 (12.4) | 60 (11.1)
Fatigue | Severe | 34 (2.1) | 5 (0.9)
Headache | Any | 440 (27.2) | 116 (21.4)
Headache | Mild | 275 (17.0) | 70 (12.9)
Headache | Moderate | 151 (9.3) | 43 (7.9)
Headache | Severe | 14 (0.9) | 3 (0.6)
Myalgia | Any | 264 (16.3) | 47 (8.7)
Myalgia | Mild | 146 (9.0) | 33 (6.1)
Myalgia | Moderate | 103 (6.4) | 12 (2.2)
Myalgia | Severe | 15 (0.9) | 2 (0.4)
Pyrexia [Pyrexia was defined as temperature ≥38.0°C (100.4°F) solicited from Day 1 through Day 5 postvaccination. Percentages are based on the number of individuals with temperature data: CAPVAXIVE, n=1,606; PNEUMOVAX 23, n=541.] | ≥38.0°C (100.4°F) | 48 (3.0) | 12 (2.2)
Pyrexia [Pyrexia was defined as temperature ≥38.0°C (100.4°F) solicited from Day 1 through Day 5 postvaccination. Percentages are based on the number of individuals with temperature data: CAPVAXIVE, n=1,606; PNEUMOVAX 23, n=541.] | ≥38.0°C (100.4°F) to <38.5°C (101.3°F) | 31 (1.9) | 4 (0.7)
Pyrexia [Pyrexia was defined as temperature ≥38.0°C (100.4°F) solicited from Day 1 through Day 5 postvaccination. Percentages are based on the number of individuals with temperature data: CAPVAXIVE, n=1,606; PNEUMOVAX 23, n=541.] | ≥38.5°C (101.3°F) to <39.0°C (102.2°F) | 11 (0.7) | 2 (0.4)
Pyrexia [Pyrexia was defined as temperature ≥38.0°C (100.4°F) solicited from Day 1 through Day 5 postvaccination. Percentages are based on the number of individuals with temperature data: CAPVAXIVE, n=1,606; PNEUMOVAX 23, n=541.] | ≥39.0°C (102.2°F) | 6 (0.4) | 6 (1.1)
Mild: does not interfere with activity; Moderate: interferes with activity; Severe: prevents daily activity

Individuals 50 Years of Age and Older Who Previously Received Pneumococcal Vaccines

Study 3 (NCT05420961) enrolled individuals 50 years of age and older who had previously received a pneumococcal vaccine at least 1 year prior to enrollment. Participants were enrolled into 1 of 3 cohorts based on their pneumococcal vaccination history (cohort 1: PNEUMOVAX 23, cohort 2: Prevnar 13, or cohort 3: PNEUMOVAX 23 followed by or preceded by Prevnar 13, PNEUMOVAX 23 preceded by VAXNEUVANCE, or VAXNEUVANCE alone). Participants in cohort 1 were randomized to receive CAPVAXIVE or VAXNEUVANCE, participants in cohort 2 were randomized to receive CAPVAXIVE or PNEUMOVAX 23, and participants in cohort 3 received CAPVAXIVE. The percentage of individuals with solicited adverse reactions that occurred within 5 days postvaccination of CAPVAXIVE or active comparator is shown in Table 3.

Table 3: Individuals with Solicited Local and Systemic Adverse Reactions Within 5 Days Postvaccination in Individuals 50 Years of Age and Older with Prior Pneumococcal Vaccination – Study 3
 |  | Cohort 1 [Cohort 1 prior vaccination with PNEUMOVAX 23] |  | Cohort 2 [Cohort 2 prior vaccination with Prevnar 13] |  | Cohort 3 [Cohort 3 prior vaccination with Prevnar 13+PNEUMOVAX 23 (n=45), or VAXNEUVANCE+PNEUMOVAX 23 (n=5), or PNEUMOVAX 23+Prevnar 13 (n=54), or VAXNEUVANCE (n=1) or Prevnar 20 (n=0)]
 |  | CAPVAXIVE n (%) | VAXNEUVANCE n (%) | CAPVAXIVE n (%) | PNEUMOVAX 23 n (%) | CAPVAXIVE n (%)
Individuals in population [Every individual is counted a single time for each applicable row and for each column.] |  | 230 | 117 | 174 | 85 | 105
Local adverse reactions [Injection-site erythema, injection-site pain, injection-site swelling, fatigue, headache, and myalgia were solicited from Day 1 through Day 5 postvaccination.] | Severity
Pain | Any | 82 (35.7) | 51 (43.6) | 72 (41.4) | 40 (47.1) | 46 (43.8)
Pain | Mild | 65 (28.3) | 43 (36.8) | 52 (29.9) | 30 (35.3) | 37 (35.2)
Pain | Moderate | 16 (7.0) | 8 (6.8) | 20 (11.5) | 10 (11.8) | 9 (8.6)
Pain | Severe | 1 (0.4) | 0 | 0 | 0 | 0
Erythema | Any | 17 (7.4) | 9 (7.7) | 13 (7.5) | 8 (9.4) | 8 (7.6)
Erythema | Mild (≤5.0 cm) | 10 (4.3) | 6 (5.1) | 5 (2.9) | 2 (2.4) | 4 (3.8)
Erythema | Moderate (>5.0 to ≤10.0 cm) | 5 (2.2) | 2 (1.7) | 6 (3.4) | 6 (7.1) | 3 (2.9)
Erythema | Severe (>10.0 cm) | 2 (0.9) | 1 (0.9) | 2 (1.1) | 0 | 1 (1.0)
Swelling | Any | 19 (8.3) | 10 (8.5) | 8 (4.6) | 14 (16.5) | 11 (10.5)
Swelling | Mild (≤5.0 cm) | 15 (6.5) | 9 (7.7) | 6 (3.4) | 7 (8.2) | 6 (5.7)
Swelling | Moderate (>5.0 to ≤10.0 cm) | 4 (1.7) | 1 (0.9) | 2 (1.1) | 7 (8.2) | 4 (3.8)
Swelling | Severe (>10.0 cm) | 0 | 0 | 0 | 0 | 1 (1.0)
Systemic adverse reactions | Severity
Fatigue | Any | 33 (14.3) | 20 (17.1) | 33 (19.0) | 11 (12.9) | 23 (21.9)
Fatigue | Mild | 25 (10.9) | 11 (9.4) | 24 (13.8) | 6 (7.1) | 19 (18.1)
Fatigue | Moderate | 8 (3.5) | 9 (7.7) | 8 (4.6) | 5 (5.9) | 4 (3.8)
Fatigue | Severe | 0 | 0 | 1 (0.6) | 0 | 0
Headache | Any | 16 (7.0) | 11 (9.4) | 18 (10.3) | 10 (11.8) | 9 (8.6)
Headache | Mild | 10 (4.3) | 9 (7.7) | 10 (5.7) | 7 (8.2) | 9 (8.6)
Headache | Moderate | 5 (2.2) | 2 (1.7) | 8 (4.6) | 3 (3.5) | 0
Headache | Severe | 1 (0.4) | 0 | 0 | 0 | 0
Myalgia | Any | 17 (7.4) | 3 (2.6) | 17 (9.8) | 8 (9.4) | 9 (8.6)
Myalgia | Mild | 9 (3.9) | 2 (1.7) | 7 (4.0) | 4 (4.7) | 7 (6.7)
Myalgia | Moderate | 8 (3.5) | 1 (0.9) | 9 (5.2) | 4 (4.7) | 2 (1.9)
Myalgia | Severe | 0 | 0 | 1 (0.6) | 0 | 0
Pyrexia [Pyrexia was defined as temperature ≥38.0°C (100.4°F) solicited from Day 1 through Day 5 postvaccination.] | ≥38.0°C (100.4°F) | 4 (1.7) | 3 (2.6) | 5 (2.9) | 1 (1.2) | 0
Pyrexia [Pyrexia was defined as temperature ≥38.0°C (100.4°F) solicited from Day 1 through Day 5 postvaccination.] | ≥38.0°C (100.4°F) to <38.5°C (101.3°F) | 2 (0.9) | 0 | 1 (0.6) | 0 | 0
Pyrexia [Pyrexia was defined as temperature ≥38.0°C (100.4°F) solicited from Day 1 through Day 5 postvaccination.] | ≥38.5°C (101.3°F) to <39.0°C (102.2°F) | 2 (0.9) | 2 (1.7) | 2 (1.1) | 1 (1.2) | 0
Pyrexia [Pyrexia was defined as temperature ≥38.0°C (100.4°F) solicited from Day 1 through Day 5 postvaccination.] | ≥39.0°C (102.2°F) | 0 | 1 (0.9) | 2 (1.1) | 0 | 0
Mild: does not interfere with activity; Moderate: interferes with activity; Severe: prevents daily activity

Safety with Concomitant Influenza Vaccine Administration

In Study 4 (NCT05526716), individuals 50 years of age and older with or without a history of prior pneumococcal vaccination were enrolled and randomized to receive either CAPVAXIVE and quadrivalent influenza vaccine [Fluzone Quadrivalent, (QIV)] concomitantly followed by placebo 30 days later (concomitant group), or QIV and placebo concomitantly followed by CAPVAXIVE 30 days later (sequential group).

In Study 4, the rates and severity of solicited systemic adverse reactions and solicited local adverse reactions at the CAPVAXIVE injection-site were similar when CAPVAXIVE was administered with or without inactivated QIV.

Serious Adverse Events

Across studies 1-4, the proportion of individuals reporting 1 or more SAEs within 1-month postvaccination was 0.3% in individuals vaccinated with CAPVAXIVE (n=14) and 0.3% in individuals vaccinated with an active comparator (n=7). The proportion of individuals reporting 1 or more SAEs within 6 months postvaccination was 1.4% in individuals vaccinated with CAPVAXIVE (n=56) and 2.0% in individuals vaccinated with an active comparator (n=40). There were no notable patterns or imbalances between vaccine groups for SAEs. Two individuals who received CAPVAXIVE had SAEs considered related to vaccination. One individual experienced an acute allergic reaction of bronchospasm (Grade 3, required medical intervention) which occurred within 30 minutes postvaccination; one individual experienced injection-site cellulitis (Grade 4, required hospitalization) on Day 6 postvaccination.

In Study 6, no SAEs were considered to be related to CAPVAXIVE.

8 USE IN SPECIFIC POPULATIONS

8.1 Pregnancy

Risk Summary

All pregnancies have a background risk of birth defect, loss, or other adverse outcomes. In the U.S. general population, the estimated background risk of major birth defects and miscarriage in clinically recognized pregnancies is 2 to 4% and 15 to 20%, respectively.

There are no adequate and well-controlled studies of CAPVAXIVE in pregnant individuals. Data on CAPVAXIVE administered to pregnant individuals are insufficient to inform vaccine-associated risks in pregnancy.

A developmental toxicity study has been performed in female rats administered 0.25 mL of a conjugated polysaccharide vaccine formulation on four occasions: twice prior to mating, once during gestation, and once during lactation. This study revealed no adverse effects on fetal or preweaning development. [See Animal Data below.]

Data

Animal Data

In a developmental toxicity study, female rats were administered 0.25 mL of a conjugated polysaccharide vaccine formulation containing the same conjugated polysaccharides as in CAPVAXIVE. Animals received 42 mcg polysaccharide per dose (a full human dose of CAPVAXIVE contains 84 mcg polysaccharide/dose) by intramuscular injection on four occasions: 28 and 7 days prior to mating, on gestation day 6, and on lactation day 7. There were no embryofetal deaths or fetal malformations, and no adverse effects on female fertility and preweaning development were observed.

8.2 Lactation

Risk Summary

Human data are not available to assess the impact of CAPVAXIVE on milk production, its presence in breast milk, or its effects on the breastfed child. The developmental and health benefits of breastfeeding should be considered along with the mother’s clinical need for CAPVAXIVE and any potential adverse effects on the breastfed child from CAPVAXIVE or from the underlying maternal condition. For preventive vaccines, the underlying condition is susceptibility to disease prevented by the vaccine.

8.4 Pediatric Use

The safety and effectiveness of CAPVAXIVE in individuals younger than 18 years of age have not been established.

8.5 Geriatric Use

Across studies 1-4, of the 4,556 individuals who received CAPVAXIVE, 1,487 individuals (32.6%) were 65 years of age and older, and 339 individuals (7.4%) were 75 years of age and older. In Study 1, of the 1,379 individuals who received CAPVAXIVE, 590 individuals (42.8%) were 65 years of age and older, and 126 individuals (9.1%) were 75 years of age and older. No clinically meaningful differences in safety of CAPVAXIVE were observed between these individuals and individuals less than 65 years of age. The opsonophagocytic activity (OPA) responses in individuals 65 years of age and older were generally lower than those observed in individuals less than 65 years of age.

8.6 Individuals Living with HIV Infection

In a double-blind descriptive study, Study 5 (NCT05393037), 313 individuals 18 years of age and older living with HIV, with CD4+ Tcells/μL ≥50 and plasma HIV ribonucleic acid (RNA) <50,000 copies/mL, with or without a history of prior pneumococcal vaccination, were randomized in a 1:1 ratio to receive either CAPVAXIVE followed by placebo 8 weeks later, or VAXNEUVANCE followed by PNEUMOVAX 23 (VAXNEUVANCE + PNEUMOVAX 23) 8 weeks later. At screening, of the participants vaccinated, 6.7% had a CD4+ T-cell counts ≥50 to <350 cells/μL, 18.6% had CD4+ Tcell counts ≥350 to <500 cells/μL, and 74.7% had CD4+ Tcell counts ≥500 cells/μL; 83% had an undetectable HIV viral load (<20 copies/mL).

The mean age of those who were randomized and vaccinated was 45.3 years and 29.2% were female. The racial distribution was as follows: 47.8% were White, 39.7% were Black or African American, 10.6% were Asian, and 0.6% were American Indian or Alaska Native; 24.4% were of Hispanic or Latino ethnicity.

Following vaccination with CAPVAXIVE, the most frequently reported (>10%) solicited adverse reactions were: injection-site pain (48.4%), fatigue (21.3%), and headache (16.8%). No SAEs were considered to be related to CAPVAXIVE.

OPA geometric mean titers (GMTs) at 1-month postvaccination in participants who received CAPVAXIVE were numerically similar to those in participants who received VAXNEUVANCE + PNEUMOVAX 23 for the 13 shared serotypes. CAPVAXIVE OPA GMTs at 1-month postvaccination were numerically higher for the 8 serotypes unique to CAPVAXIVE compared with VAXNEUVANCE + PNEUMOVAX 23. The effectiveness of CAPVAXIVE in individuals with HIV has not been established.

11 DESCRIPTION

CAPVAXIVE (Pneumococcal 21-valent Conjugate Vaccine) is an injection for intramuscular use. CAPVAXIVE is a sterile solution of purified capsular polysaccharides from S. pneumoniae serotypes 3, 6A, 7F, 8, 9N, 10A, 11A, 12F, 15A, 15B (de-O-acetylated prior to conjugation), 16F, 17F, 19A, 20A, 22F, 23A, 23B, 24F, 31, 33F, and 35B individually conjugated to CRM197 carrier protein. CRM197 is a nontoxic mutant of diphtheria toxin (originating from Corynebacterium diphtheriae C7) expressed recombinantly in Pseudomonas fluorescens.

Each S. pneumoniae serotype is grown separately in media containing yeast extract, dextrose, salts, and soy peptone. The pneumococcal bacteria are inactivated after growth by addition of phenol to the culture media. Subsequently, each polysaccharide is purified to produce a powder using a series of chemical and physical methods. Serotype 15B polysaccharide is de-O-acetylated (deOAc 15B). The purified polysaccharides are chemically activated. Recombinant P. fluorescens expressing CRM197 is grown in a glycerol-based, chemically-defined salt medium. The CRM197 is then purified by chromatography and ultrafiltration. Each polysaccharide is individually conjugated to CRM197 carrier protein to create 21 individual conjugates. The final vaccine is prepared by blending the 21 conjugated polysaccharides in a final buffer containing histidine, polysorbate 20, and sodium chloride.

Each 0.5 mL dose contains a total of 84 mcg of pneumococcal polysaccharide antigen (4 mcg each of polysaccharide serotypes 3, 6A, 7F, 8, 9N, 10A, 11A, 12F, 15A, 15B (deOAc 15B), 16F, 17F, 19A, 20A, 22F, 23A, 23B, 24F, 31, 33F, and 35B) conjugated to approximately 65 mcg of CRM197 carrier protein, 1.55 mg L-histidine, 0.50 mg of polysorbate 20, 4.49 mg sodium chloride, and water for injection.

CAPVAXIVE does not contain any preservatives.

12 CLINICAL PHARMACOLOGY

12.1 Mechanism of Action

Protection against invasive pneumococcal disease is conferred mainly by opsonophagocytic killing of S. pneumoniae. CAPVAXIVE induces OPA against 22 S. pneumoniae serotypes. The de-O-acetylated polysaccharide from serotype 15B has a molecular structure similar to the polysaccharide from serotype 15C and induces OPA to serotype 15C. The deOAc15B also induces cross-reactive OPA against serotype 15B. An OPA titer that is predictive of protection against invasive pneumococcal disease or pneumococcal pneumonia has not been established.

13 NONCLINICAL TOXICOLOGY

13.1 Carcinogenesis, Mutagenesis, Impairment of Fertility

CAPVAXIVE has not been evaluated for carcinogenic or mutagenic potential or for impairment of male fertility in animals.

14 CLINICAL STUDIES

For studies 1-4, immunogenicity was assessed by serotype-specific opsonophagocytic activity (OPA) responses at 1-month postvaccination. The primary immunogenicity endpoints included OPA geometric mean titers (GMTs) and the proportion of individuals who achieved ≥4-fold rise in OPA responses from prevaccination to 1-month postvaccination.

14.1 Individuals 18 years of age and older

The effectiveness of CAPVAXIVE in individuals 18 years of age and older for the prevention of invasive disease caused by S. pneumoniae serotypes 3, 6A, 7F, 8, 9N, 10A, 11A, 12F, 15A, 15B, 15C, 16F, 17F, 19A, 20A, 22F, 23A, 23B, 24F, 31, 33F and 35B and for the prevention of pneumonia caused by S. pneumoniae serotypes 3, 6A, 7F, 8, 9N, 10A, 11A, 12F, 15A, 15C, 16F, 17F, 19A, 20A, 22F, 23A, 23B, 24F, 31, 33F, and 35B was demonstrated based on comparative immunogenicity to a licensed pneumococcal vaccine (Prevnar 20).

Pneumococcal Vaccine-Naïve Individuals 50 years of age and older

In Study 1, 2,362 pneumococcal vaccine-naïve individuals 50 years of age and older were randomized to receive either CAPVAXIVE or Prevnar 20. [See Adverse Reactions (6.1).]

Table 4 summarizes the 21 serotype-specific OPA geometric mean antibody titers (GMTs) at 30 days postvaccination. The study demonstrated that CAPVAXIVE is noninferior to Prevnar 20 for the 10 shared serotype polysaccharides and induces statistically significantly greater OPA GMTs compared with Prevnar 20 for 10 of 11 serotype polysaccharides unique to CAPVAXIVE. Serotype 15C did not meet the criterion for statistical significance.

Table 5 summarizes the proportion of individuals who achieved a ≥4-fold rise from prevaccination to 1-month postvaccination for OPA responses. For 10 of 11 serotype polysaccharides unique to CAPVAXIVE, CAPVAXIVE induced statistically significantly greater OPA responses compared with Prevnar 20. Serotype 15C did not meet the criterion for statistical significance.

Table 4: Serotype-Specific OPA GMTs in Pneumococcal Vaccine-Naïve Individuals 50 Years of Age and Older (Study 1)
Pneumococcal Serotype | CAPVAXIVE (N = 1179) |  | Prevnar 20 (N = 1177) |  | GMT Ratio [GMTs, GMT ratio, and 95% CI were estimated from a constrained Longitudinal Data Analysis model.] (CAPVAXIVE/Prevnar 20) (95% CI)
 | n | GMT | n | GMT
10 Shared Serotypes [Non-inferiority for the serotypes shared by CAPVAXIVE and Prevnar 20 was based on the lower bound of the 2-sided 95% CI for the estimated GMT ratio (CAPVAXIVE/Prevnar 20) being >0.5.]
3 | 1154 | 274.0 | 1161 | 176.7 | 1.55 (1.40, 1.72)
6A | 1148 | 2302.0 | 1153 | 2972.5 | 0.77 (0.68, 0.88)
7F | 1152 | 3637.4 | 1158 | 3429.9 | 1.06 (0.95, 1.18)
8 | 1155 | 2501.3 | 1158 | 1811.1 | 1.38 (1.25, 1.53)
10A | 1161 | 3893.4 | 1159 | 4678.0 | 0.83 (0.75, 0.93)
11A | 1145 | 3232.6 | 1150 | 2092.8 | 1.54 (1.39, 1.72)
12F | 1160 | 2641.2 | 1161 | 2499.6 | 1.06 (0.92, 1.21)
19A | 1159 | 2136.1 | 1162 | 2817.8 | 0.76 (0.69, 0.84)
22F | 1147 | 3874.5 | 1154 | 4770.1 | 0.81 (0.72, 0.92)
33F | 1154 | 13558.9 | 1157 | 11742.1 | 1.15 (1.01, 1.32)
11 Serotypes Unique to CAPVAXIVE [Statistically significantly greater OPA responses for the serotypes unique to CAPVAXIVE compared with Prevnar 20 were based on the lower bound of the 2-sided 95% CI for the estimated GMT ratio (CAPVAXIVE/Prevnar 20) being >2.0.]
9N | 1147 | 7470.7 | 1150 | 1640.4 | 4.55 (4.12, 5.04)
15A | 1107 | 5237.2 | 1102 | 1589.0 | 3.30 (2.91, 3.74)
15C | 1153 | 4216.2 | 1158 | 2072.3 | 2.03 (1.77, 2.34)
16F | 1151 | 4868.2 | 1153 | 846.3 | 5.75 (5.16, 6.41)
17F | 1148 | 7764.9 | 1156 | 460.4 | 16.86 (14.90, 19.09)
20A | 1161 | 6099.2 | 1155 | 631.1 | 9.66 (8.66, 10.79)
23A | 1132 | 3737.2 | 1104 | 461.5 | 8.10 (6.86, 9.55)
23B | 1160 | 1082.5 | 1160 | 107.3 | 10.09 (8.48, 12.00)
24F | 1153 | 2728.6 | 1130 | 70.5 | 38.71 (33.87, 44.25)
31 | 1153 | 3132.5 | 1154 | 144.4 | 21.69 (18.68, 25.18)
35B | 1153 | 8527.8 | 1159 | 1383.0 | 6.17 (5.59, 6.80)
N=Number of individuals randomized and vaccinated; n=Number of individuals contributing to the analysis.

Table 5: Pneumococcal Vaccine-Naïve Individuals 50 years of Age and Older With a ≥4-Fold Rise in OPA Responses for Serotypes Unique to CAPVAXIVE (Study 1)
Pneumococcal Serotype | CAPVAXIVE (N=1179) | Prevnar 20 (N=1177) | Percentage Point Difference (CAPVAXIVE – Prevnar 20)
Pneumococcal Serotype | Observed Response Percentage (m/n) | Observed Response Percentage (m/n) | Estimate (95% CI) [Estimated difference and CI were based on the stratified Miettinen & Nurminen method.] , [Statistically significantly greater OPA responses were based on the lower bound of the 2-sided 95% CI of the differences (CAPVAXIVE – Prevnar 20) between the percentages of individuals with a ≥4-fold rise from prevaccination to 1-month postvaccination being >10 percentage points.]
9N | 64.7 (595/920) | 19.9 (195/978) | 44.7 (40.7, 48.6)
15A | 66.7 (462/693) | 35.8 (253/706) | 30.9 (25.8, 35.8)
15C | 83.4 (794/952) | 74.2 (695/937) | 9.2 (5.6, 12.9)
16F | 71.9 (654/910) | 20.8 (200/961) | 51.1 (47.1, 54.9)
17F | 75.8 (653/862) | 9.5 (90/952) | 66.3 (62.8, 69.6)
20A | 67.3 (675/1003) | 9.6 (97/1011) | 57.7 (54.2, 61.1)
23A | 78.9 (598/758) | 36.8 (270/734) | 42.2 (37.6, 46.6)
23B | 85.5 (873/1021) | 49.6 (506/1021) | 35.9 (32.1, 39.6)
24F | 80.5 (745/925) | 6.3 (55/872) | 74.2 (71.1, 77.1)
31 | 76.5 (698/912) | 17.9 (171/954) | 58.6 (54.8, 62.1)
35B | 60.0 (550/917) | 6.8 (67/988) | 53.2 (49.6, 56.6)
N=Number of individuals randomized and vaccinated; m=Number of individuals with the indicated response; n=Number of individuals contributing to the analysis

In Study 1, 64.7% of individuals 50 years of age and older, who received CAPVAXIVE, had ≥4-fold rise in cross-reactive OPA titers for serotype 15B, which met the prespecified success criterion (lower bound of the 2-sided 95% CI of the proportion of individuals with a ≥4-fold rise in OPA responses is >50%). In a descriptive analysis, the S. pneumoniae serotype 15B OPA GMT was 4,400.6 following administration of CAPVAXIVE, and 4,640.0 following administration of Prevnar 20, with a GMT ratio of 0.95 (95% CI: 0.84, 1.07).

Pneumococcal Vaccine-Naïve Individuals 18 through 49 Years of Age

In Study 1, pneumococcal vaccine-naïve individuals 18 through 49 years of age were randomized in a 2:1 ratio to receive CAPVAXIVE or Prevnar 20. [See Adverse Reactions (6.1).]

Effectiveness of CAPVAXIVE in individuals 18 through 49 years of age was assessed by a comparison of the OPA responses induced by CAPVAXIVE in this age group to the OPA responses of individuals 50 through 64 years of age. The OPA responses of individuals 18 through 49 years of age to each of 22 S. pneumoniae serotypes met the criteria for immunobridging as the lower bound of the 2-sided 95% CI for the GMT ratio for each serotype was >0.5 (see Table 6). The S. pneumoniae serotype 15B cross-reactive OPA GMT was 10,976.7 following administration of CAPVAXIVE in individuals 18 through 49 years of age and 5,438.9 following administration of CAPVAXIVE in individuals 50 through 64 years of age, with a GMT ratio of 2.02 (95% CI: 1.57, 2.60).

Table 6: Comparison of Serotype-Specific OPA GMTs in Pneumococcal Vaccine-Naïve Individuals 18 through 49 Years of Age to 50 through 64 Years of Age Who Received CAPVAXIVE (Study 1)
Pneumococcal Serotype | 18 through 49 years (N = 200) |  | 50 through 64 years (N = 589) |  | GMT Ratio [GMTs, GMT ratio, and 95% CI were estimated from a Longitudinal Data Analysis model.] , [Immunobridging was based on the lower bound of the 2-sided 95% CI for the estimated GMT ratio (18 through 49 years / 50 through 64 years) being >0.5.] (18 through 49 years / 50 through 64 years) (95% CI)
 | n | GMT | n | GMT
3 | 194 | 308.6 | 572 | 282.7 | 1.09 (0.90, 1.33)
6A | 196 | 5289.6 | 569 | 2572.9 | 2.06 (1.61, 2.62)
7F | 198 | 6447.2 | 571 | 4278.8 | 1.51 (1.23, 1.84)
8 | 197 | 4516.0 | 571 | 3004.7 | 1.50 (1.26, 1.79)
9N | 197 | 17283.2 | 570 | 8791.4 | 1.97 (1.59, 2.43)
10A | 197 | 6808.1 | 575 | 4382.6 | 1.55 (1.26, 1.92)
11A | 196 | 5871.6 | 564 | 3785.8 | 1.55 (1.26, 1.91)
12F | 196 | 6150.4 | 574 | 3561.2 | 1.73 (1.37, 2.17)
15A | 184 | 11319.2 | 550 | 5901.2 | 1.92 (1.55, 2.37)
15C | 195 | 10194.0 | 570 | 5708.0 | 1.79 (1.36, 2.35)
16F | 193 | 8877.0 | 571 | 5720.0 | 1.55 (1.26, 1.91)
17F | 194 | 16070.6 | 568 | 10068.0 | 1.60 (1.26, 2.02)
19A | 198 | 2773.2 | 574 | 2374.6 | 1.17 (0.97, 1.40)
20A | 197 | 13150.0 | 575 | 7562.7 | 1.74 (1.39, 2.18)
22F | 198 | 9299.6 | 568 | 4683.6 | 1.99 (1.58, 2.49)
23A | 192 | 8848.7 | 561 | 4739.5 | 1.87 (1.43, 2.44)
23B | 198 | 2140.1 | 575 | 1420.9 | 1.51 (1.11, 2.04)
24F | 197 | 4137.6 | 570 | 3047.2 | 1.36 (1.10, 1.67)
31 | 195 | 8005.6 | 570 | 3820.7 | 2.10 (1.63, 2.69)
33F | 197 | 34805.5 | 570 | 17607.4 | 1.98 (1.52, 2.57)
35B | 198 | 13933.4 | 573 | 9053.9 | 1.54 (1.26, 1.87)
N=Number of individuals randomized and vaccinated; n=Number of individuals contributing to the analysis.

Individuals 50 years of age and older with Prior Pneumococcal Vaccination

Study 3, a descriptive Phase 3 study, enrolled individuals 50 years of age and older who were previously vaccinated with other pneumococcal vaccines at least 1 year prior to study entry. Participants were enrolled into 1 of 3 cohorts based on their pneumococcal vaccination history (cohort 1: PNEUMOVAX 23, cohort 2: Prevnar 13, or cohort 3: PNEUMOVAX 23 followed by or preceded by Prevnar 13, PNEUMOVAX 23 preceded by VAXNEUVANCE, or VAXNEUVANCE alone).

Participants in cohort 1 were randomized to receive CAPVAXIVE (n=231) or VAXNEUVANCE (n=119), participants in cohort 2 were randomized to receive CAPVAXIVE (n=176) or PNEUMOVAX 23 (n=85), and participants in cohort 3 were allocated to receive CAPVAXIVE (n=106).

In each of the 3 cohorts, serotype-specific OPA GMTs and the proportion of individuals with ≥4-fold rise in OPA responses from baseline to 1-month postvaccination were assessed. In Cohort 1, CAPVAXIVE elicited OPA responses that were comparable to VAXNEUVANCE for the 6 shared serotypes, and higher for the 15 unique serotypes and serotype 15B. In Cohort 2, CAPVAXIVE elicited OPA responses comparable to PNEUMOVAX 23 for the 12 shared serotypes and serotype 15B, and higher for the 9 unique serotypes. OPA responses to CAPVAXIVE were similar across the 3 cohorts of participants who previously received one or more pneumococcal vaccines.

Individuals 18 through 64 years of age at Increased Risk of Pneumococcal Disease due to Certain Medical Conditions

In a double-blind descriptive study, Study 6, 518 pneumococcal vaccine-naïve individuals 18 years through 64 years of age at increased risk of pneumococcal disease due to one or more prespecified medical conditions were randomized in a 3:1 ratio to receive either CAPVAXIVE followed by placebo 8 weeks later, or VAXNEUVANCE followed by PNEUMOVAX 23 (VAXNEUVANCE + PNEUMOVAX 23) 8 weeks later. Among the vaccinated participants with one condition increasing the risk of pneumococcal disease, 194 (37.6%) had diabetes mellitus, 99 (19.2%) had chronic lung disease, 84 (16.3%) had chronic heart disease, 34 (6.6%) had chronic liver disease, and 23 (4.5%) had chronic kidney disease. 82 (15.9%) participants had ≥2 increased risk conditions.

OPA GMTs at 1-month postvaccination in participants who received CAPVAXIVE were numerically similar to those in participants who received VAXNEUVANCE + PNEUMOVAX 23 for the 13 shared serotypes. CAPVAXIVE OPA GMTs at 1-month postvaccination were numerically higher for the 8 serotypes unique to CAPVAXIVE compared with VAXNEUVANCE + PNEUMOVAX 23.

14.2 Concomitant Vaccination

In a double-blind study (Study 4), 1,080 individuals 50 years of age and older, with or without a history of prior pneumococcal vaccination, were randomized in a 1:1 ratio. One vaccination group received CAPVAXIVE and QIV concomitantly, followed by placebo 30 days later (concomitant group). A second vaccination group received QIV and placebo concomitantly, followed by CAPVAXIVE 30 days later (sequential group). Antibody responses were assessed 1-month postvaccination.

The OPA responses to CAPVAXIVE administered concomitantly with QIV were non-inferior to the OPA responses to CAPVAXIVE administered sequentially after QIV for 20 of 21 serotypes [lower bound of the 2-sided 95% CI of the GMT ratio (concomitant group/sequential group) was >0.5]; the non-inferiority was not met for serotype 23B [lower bound of the 2-sided 95% CI of the GMT ratio (concomitant group/sequential group) was 0.44]. The OPA response to serotype 15B was not assessed for non-inferiority. In a descriptive analysis, the OPA GMT in the concomitant group was 3,438.7 and in the sequential group was 4,440.5, with a GMT ratio of 0.77 (95% CI: 0.64, 0.94). The influenza strain-specific hemagglutination inhibition (HAI) responses to QIV administered concomitantly with CAPVAXIVE were non-inferior to the HAI responses to QIV administered alone for 3 of 4 influenza strains [lower bound of the 2-sided 95% CIs for HAI GMT ratios (concomitant group/sequential group) was >0.67 (non-inferiority margin); the lower bound was 0.67 for the A/H3N2 influenza strain].

16 HOW SUPPLIED/STORAGE AND HANDLING

CAPVAXIVE is supplied as follows:

NDC 0006-4347-01: Carton of one single-dose prefilled Luer Lock syringe with tip cap, containing 1 dose of 0.5 mL (NDC 0006-4347-99).

NDC 0006-4347-02: Carton of ten single-dose prefilled Luer Lock syringes with tip caps, each syringe containing 1 dose of 0.5 mL (NDC 0006-4347-99).

STORAGE AND HANDLING

Store refrigerated at 2°C to 8°C (36°F to 46°F).

Do not freeze. Protect from light.

The tip cap and plunger stopper are not made with natural rubber latex.

17 PATIENT COUNSELING INFORMATION

Advise the patient to read the FDA-approved patient labeling (Patient Information).

- Inform the patient of the benefits and risks associated with vaccination with CAPVAXIVE.
- Inform the patient that vaccination with CAPVAXIVE may not protect all vaccine recipients.
- Instruct the patient to report any adverse reactions to their healthcare provider or to the vaccine manufacturer or the U.S. Department of Health and Human Services through the Vaccine Adverse Event Reporting System (VAERS), 1-800-822-7967, or report online at www.vaers.hhs.gov.

Manufactured by: Merck Sharp & Dohme LLC
Rahway, NJ 07065, USA

U.S. license number 0002

For patent information: www.msd.com/research/patent

The trademarks depicted herein are owned by their respective companies.

Copyright © 2024-2025 Merck & Co., Inc., Rahway, NJ, USA, and its affiliates.
All rights reserved.

uspi-v116-i-2507r001

Patient Information
CAPVAXIVE™ (pronounced “Cap-VACKS-iv”)
(Pneumococcal 21-valent Conjugate Vaccine)

Before you get CAPVAXIVE, read this information sheet and be sure you understand it. If you have questions or experience any side effects, talk to your healthcare provider. This information does not take the place of talking about CAPVAXIVE with your healthcare provider. Your healthcare provider will decide if CAPVAXIVE is right for you.

What is CAPVAXIVE?

- CAPVAXIVE is a vaccine for individuals 18 years of age and older to help protect against invasive pneumococcal disease and pneumonia caused by certain types of bacteria called pneumococcus.
- These bacteria can cause many types of illnesses, which can be severe, such as infections in:
  - your lungs (pneumonia)
  - the area around your brain and spinal cord (meningitis)
  - your blood (bacteremia)
- You cannot get pneumococcal disease from CAPVAXIVE.
- CAPVAXIVE might not protect everyone who gets the vaccine.

Who should not get CAPVAXIVE?
Do not get CAPVAXIVE if you had an allergic reaction to any of its ingredients, including diphtheria toxoid. (See the list of ingredients at the end of this information sheet.)

What should I tell my healthcare provider before getting CAPVAXIVE?
Tell your healthcare provider if you:

- have had an allergic reaction to any vaccine.
- are taking any medications or treatments that might weaken the immune system (like immunosuppressants or steroids).
- have a weak immune system (which means your body is less able to fight off infections).
- are pregnant or planning to become pregnant.
- are breastfeeding or plan to breastfeed.

How is CAPVAXIVE given?

- You will get an injection into the muscle (usually in your upper arm).
- You will get one dose of the vaccine.

What are the possible side effects of CAPVAXIVE?
The most common side effects of CAPVAXIVE are:

- Pain, redness, or swelling where you got the injection
- Feeling tired
- Headache
- Muscle aches
- Fever

These side effects usually last less than 3 days.
Tell your healthcare provider about these side effects or any unusual symptoms that develop after you get this vaccine. Get medical care right away if you have symptoms of an allergic reaction, which may include:

- Wheezing or trouble breathing
- Swelling of the face, lips, or tongue
- Hives
- Rash

There may be side effects not listed here. Ask your healthcare provider for more information.
You may also report any side effects to Merck Sharp & Dohme LLC at 1-877-888-4231 or directly to Vaccine Adverse Event Reporting System (VAERS). The VAERS toll-free number is 1-800-822-7967 or report online to www.vaers.hhs.gov.

Where can I get more information about CAPVAXIVE?
You can ask your pharmacist or healthcare provider for more information about CAPVAXIVE.

What are the ingredients in CAPVAXIVE?

Active ingredient(s): Bacterial sugars from 21 types of pneumococcus; each linked to a protein (CRM197). The sugars from these bacteria and the protein are not alive and do not cause disease.
Inactive ingredient(s): L-histidine, polysorbate 20, sodium chloride, water.
CAPVAXIVE does not have any preservatives.
The tip cap and plunger stopper of the prefilled syringe are not made with natural rubber latex.

Manufactured by: Merck Sharp & Dohme LLC, Rahway, NJ 07065, USA

For patent information: www.msd.com/research/patent. The trademarks depicted herein are owned by their respective companies.

Copyright © 2024 Merck & Co., Inc., Rahway, NJ, USA, and its affiliates. All rights reserved.

usppi-v116-i -2406r000

This Patient Information has been approved by the U.S. Food and Drug Administration

Issued: 06/2024

PRINCIPAL DISPLAY PANEL - 0.5 mL Syringe carton

NDC 0006-4347-01
1 Single-dose 0.5 mL Syringe

REFRIGERATE

Pneumococcal 21-valent
Conjugate Vaccine

CAPVAXIVE™

For use in individuals 18 years of age
and older.

For intramuscular use

Rx only

PRINCIPAL DISPLAY PANEL - 0.5 mL Syringe carton

NDC 0006-4347-02
10 Single-dose 0.5-mL Syringes

REFRIGERATE

Pneumococcal 21-valent
Conjugate Vaccine

CAPVAXIVE™

For intramuscular use

For use in individuals 18 years of age
and older.

Rx only